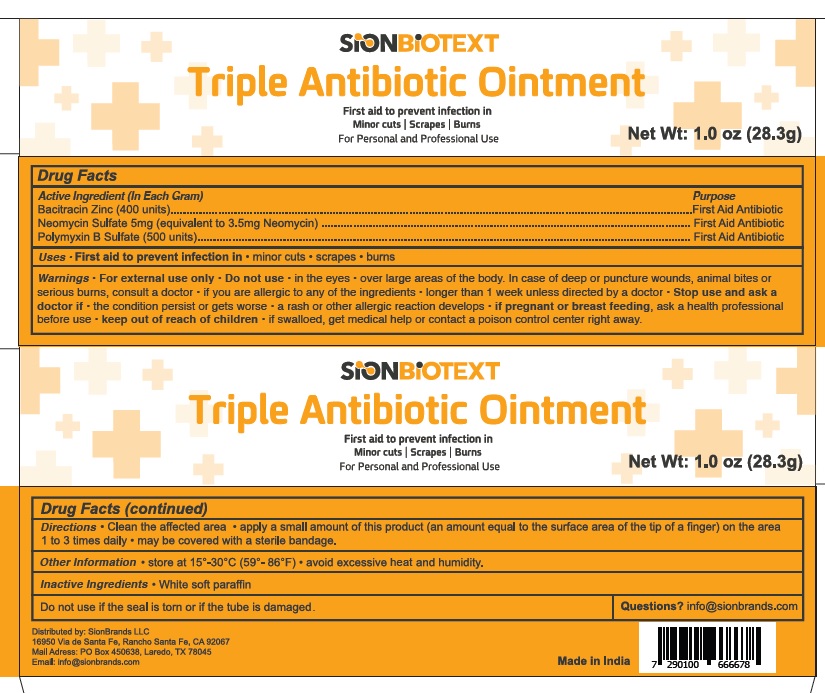 DRUG LABEL: SionBiotext Triple Antibiotic
NDC: 68786-400 | Form: OINTMENT
Manufacturer: Sion Biotext Medical Ltd
Category: otc | Type: HUMAN OTC DRUG LABEL
Date: 20250513

ACTIVE INGREDIENTS: BACITRACIN ZINC 400 [USP'U]/1 g; NEOMYCIN SULFATE 0.0035 g/1 g; POLYMYXIN B SULFATE 500 [USP'U]/1 g
INACTIVE INGREDIENTS: WHITE PETROLATUM

drug facts

Active Ingredient (In Each Gram)

Bacitracin Zinc (400 units)

Neomycin sulfate 5mg (equivalent to 3.5 mg Neomycin)

Polymyxin B sulfate (500 units)

Purpose

First Aid Antibiotic

Uses

First aid to prevent infection in

- minor cuts
- scrapes
- burns

Warnings

For external use only.

Do not use

- in the eyes
- over large areas of the body
- In case of deep or puncture wounds, animal bites, or serious burns,
- consult a doctor: if you are allergic to any of the ingredients
- longer than 1 week unless directed by a doctor
- if the seal is torn or if the tube is damaged

Stop use and ask a doctor if

- if condition persists or gets worse
- a rash or other allergic reaction develops

If pregnant or breast feeding

ask a health professional before use

keep out of reach of children

If swalloed, get medical help or contact a poison control center right away

Directions

- Clean the affected area
- apply a small amount of this product (an amount equal to the surface area of the tip of a finger) on the area 1 to 3 times daily
- may be covered with a sterile bandage

Other Information

- Store at 15°-30°C (59°-86°F)
- avoid excessive heat and humidity

Inactive Ingredients

White soft paraffin

Questions

info@sionbrands.com

Other Information

Distributed by: SionBrands LLC

16950 Via de Santa Fe, Rancho Santa Fe, CA 92067

Mail Address: PO Box 450638, Laredo, TX 78045

Email: info@sionbrands.com

Made in India

PACKAGE LABEL

NDC 68786-400-28

SionBiotext

Triple Antibiotic Ointment

First aid to prevent infection in Minor cuts | Scrapes | Burns

For Personal and Professional Use

Net. Wt: 1.0 oz (28.3g)